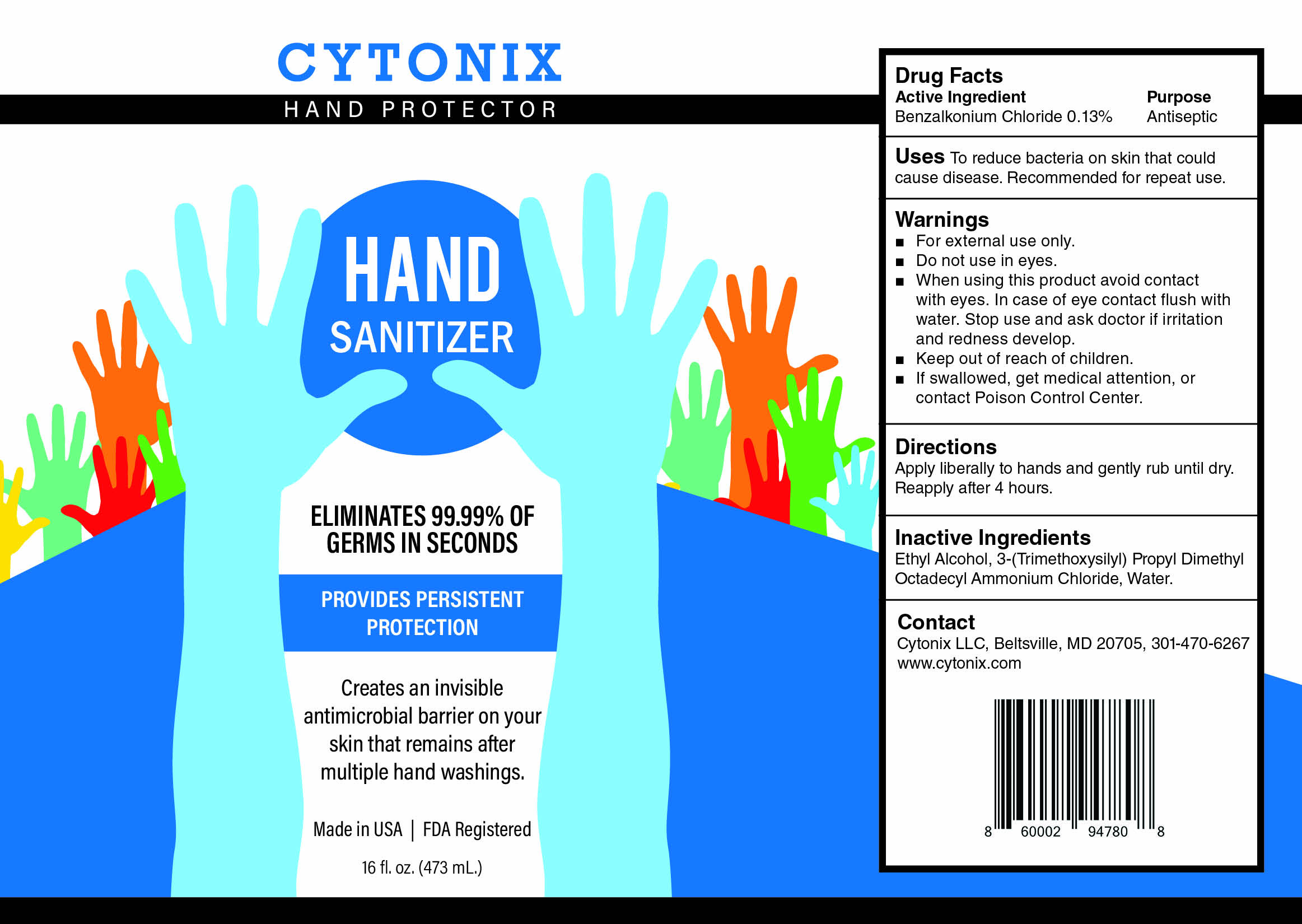 DRUG LABEL: Hand Protector
NDC: 79291-653 | Form: SOLUTION
Manufacturer: Cytonix, LLC
Category: otc | Type: HUMAN OTC DRUG LABEL
Date: 20200915

ACTIVE INGREDIENTS: BENZALKONIUM CHLORIDE 0.13 g/100 mL
INACTIVE INGREDIENTS: WATER 84 g/100 mL

ACTIVE INGREDIENT

Benzalkonium Chloride 0.13%

Purpose: Antiseptic. Hand and skin sanitizer.

INDICATIONS AND USAGE

USES: to reduce bacteria on skin that could cause disease. Recommended for repeat use.

WARNINGS

For external use only.
Do not use in eyes.
When using this product avoid contact with eyes. In case of eye contact flush with water. Stop use and ask doctor if irritation and redness develop.
Keep out of reach of children.
If swallowed, get medical attention or contact a Poison Control Center.

Keep out of reach of children.

WHEN USING

Avoid contact with eyes. In case of eye contact flush with plenty of water.

Stop use and ask doctor if irritation or redness develop.

INACTIVE INGREDIENT

3-(trimethoxysilyl) Propyl Dimethyl Octadecyl Ammonium Chloride, Ethyl Alcohol, Water

DOSAGE AND ADMINISTRATION

Apply liberally to hands and gently rub until dry. Reapply after 4 hours.

QUESTIONS

Contact:

Cytonix LLC, Beltsville, MD

20705 USA 301-470-6267

www.cytonix.com

Hand Protector label 79291-653-03 16oz (473mL)